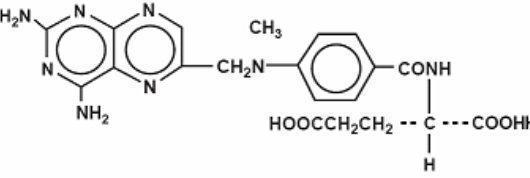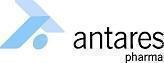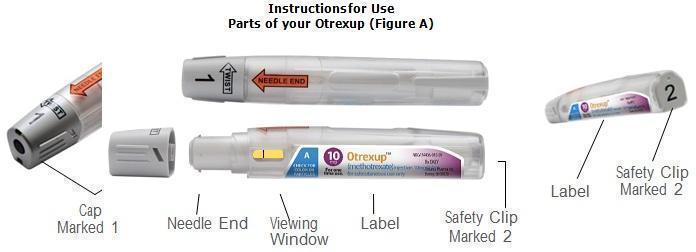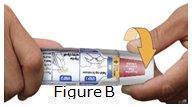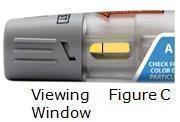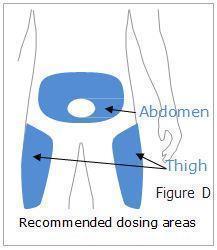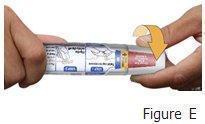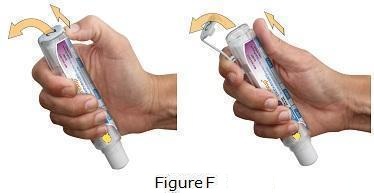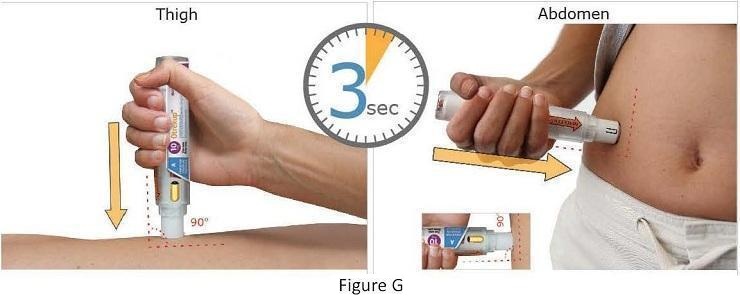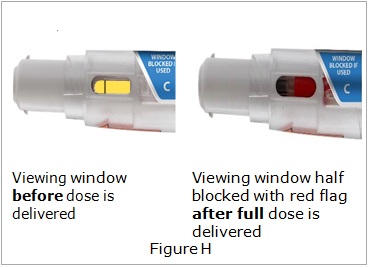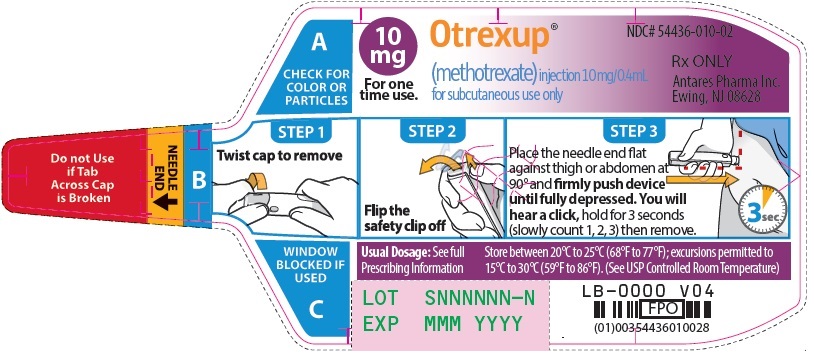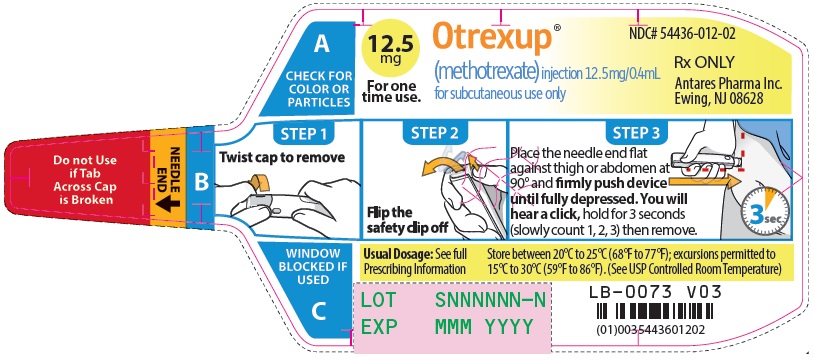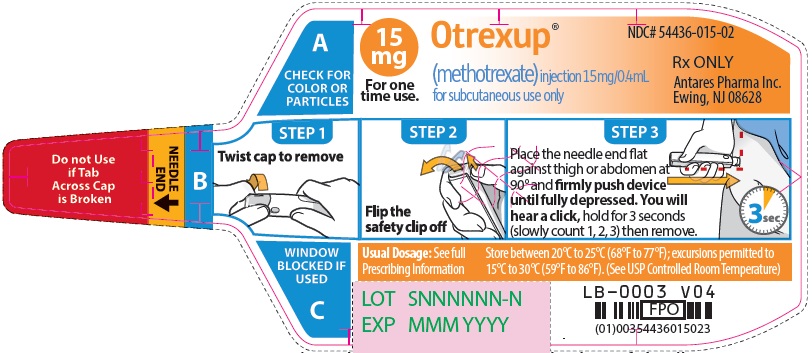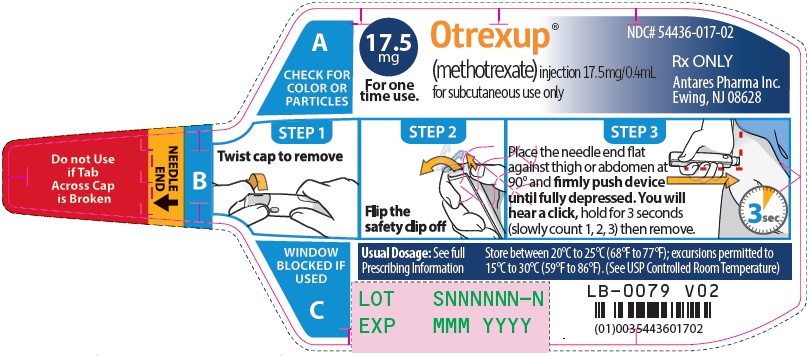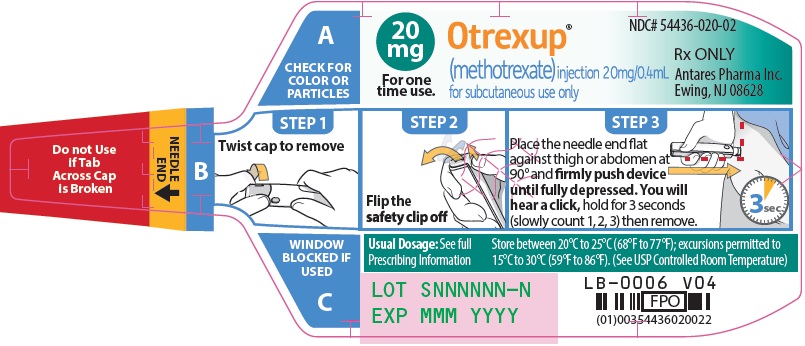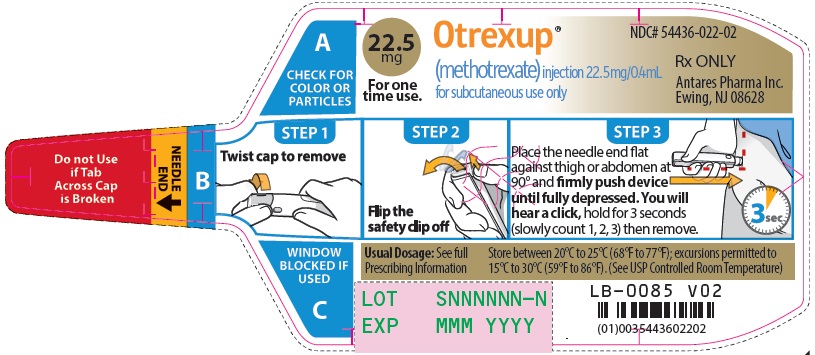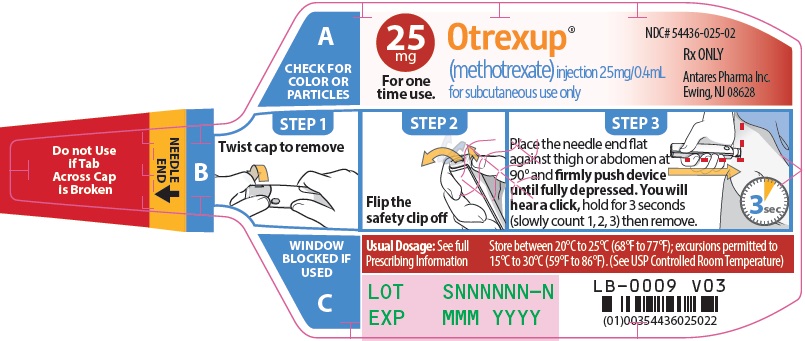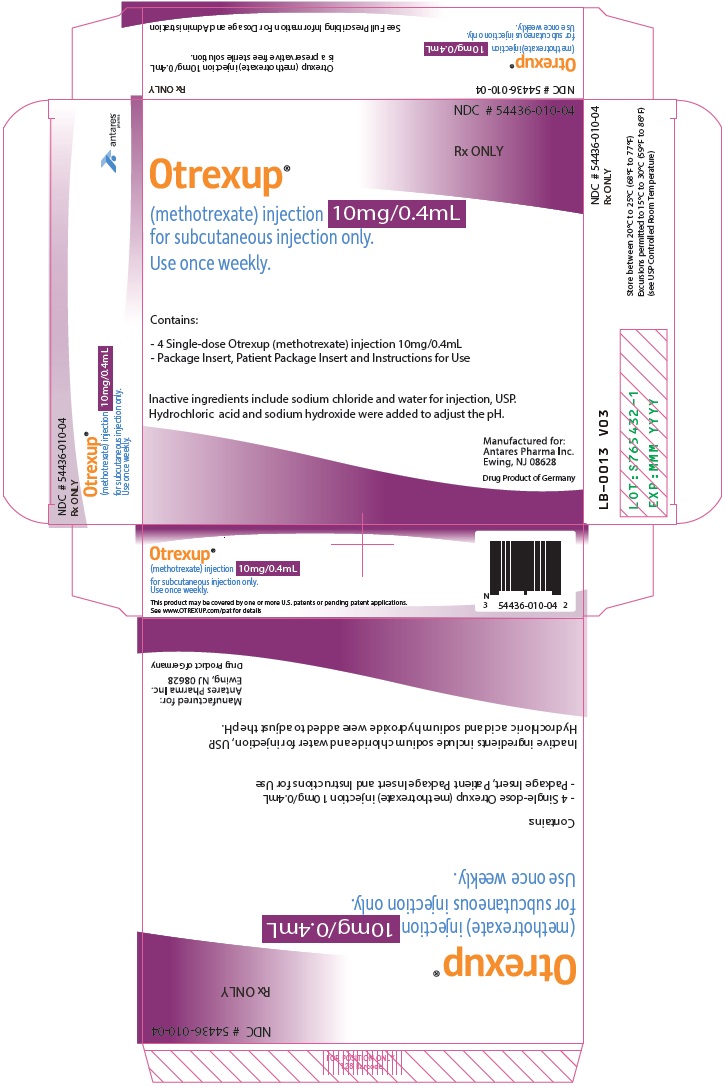 DRUG LABEL: Otrexup
NDC: 54436-075 | Form: INJECTION, SOLUTION
Manufacturer: Antares Pharma, Inc.
Category: prescription | Type: HUMAN PRESCRIPTION DRUG LABEL
Date: 20250131

ACTIVE INGREDIENTS: METHOTREXATE 7.5 mg/0.4 mL
INACTIVE INGREDIENTS: SODIUM CHLORIDE; WATER

HIGHLIGHTS OF PRESCRIBING INFORMATION

These highlights do not include all the information needed to use OTREXUP™safely and effectively. See full prescribing information for OTREXUP.
OTREXUP (methotrexate) injection, for subcutaneous use
Initial U.S. Approval: 1953

WARNING: SEVERE TOXIC REACTIONS, INCLUDING EMBRYO-FETAL TOXICITY AND DEATH

See full prescribing information for complete boxed warning.

• Serious toxic reactions and death have been reported with the use of methotrexate. Patients should be closely monitored for bone marrow, liver, lung, skin, and kidney toxicities (5.1).

• Methotrexate can cause embryo-fetal toxicity, including fetal death. Use is contraindicated during pregnancy (4). Advise females and males of reproductive potential to use effective contraception during and after treatment with methotrexate (5.2, 8.1, 8.3).

• Unexpectedly severe (sometimes fatal) bone marrow suppression, aplastic anemia, and gastrointestinal toxicity have been reported with concomitant administration of methotrexate (usually in high dosage) along with somenonsteroidalanti-inflammatory drugs (NSAIDs) (5.1).

• Hepatotoxicity, fibrosis, and cirrhosis may occur after prolonged use (5.1).

• Methotrexate may cause interstitial pneumonitis at any time during therapy and has been reported at low doses. Pulmonary symptoms (especially a dry, nonproductive cough) may require interruption of treatment and careful investigation (5.1).

• Diarrhea, ulcerative stomatitis, hemorrhagic enteritis, and death from intestinal perforation may occur (5.1).

• Severe, occasionally fatal, skin reactions have been reported (5.1).

• Potentially fatal opportunistic infections may occur (5.1).

1 INDICATIONS AND USAGE

Otrexup is a folate analog metabolic inhibitor indicated for the:

• Management of patients with severe, active rheumatoid arthritis (RA) and polyarticular juvenile idiopathic arthritis (pJIA), who are intolerant of or had an inadequate response to first-line therapy (1.1).

• Symptomatic control of severe, recalcitrant, disabling psoriasis in adults who are not adequately responsive to other forms of therapy (1.2).

Limitation of Use

Otrexup is not indicated for the treatment of neoplastic diseases (1.3).

2 DOSAGE AND ADMINISTRATION

- Otrexup is for once weekly subcutaneous use only. Administer Otrexup in the abdomen or thigh. (2.1).
- Use another formulation of methotrexate for patients requiring oral, intramuscular, intravenous, intra-arterial, or intrathecal dosing, doses less than 10 mg per week, doses above 25 mg per week, high-dose regimens, or dose adjustments of less than 5 mg increments (2.1).
- Starting doses of methotrexate:
  - RA: 7.5 mg once weekly (2.2).
  - pJIA: 10 mg/m^2once weekly (2.2).
  - Psoriasis: 10 to 25 mg once weekly of an oral, intramuscular, subcutaneous, or intravenous formulation (2.3).
- Adjust dose gradually to achieve an optimal response (2.2, 2.3).

3 DOSAGE FORMS AND STRENGTHS

Injection: Single-dose auto-injector delivering 0.4 mL of methotrexate in the following dosage strengths: 10 mg, 12.5 mg, 15 mg, 17.5 mg, 20 mg, 22.5 mg and 25 mg (3).

4 CONTRAINDICATIONS

- Pregnancy (4)
- Alcoholism or liver disease (4)
- Immunodeficiency syndromes (4)
- Preexisting blood dyscrasias (4)
- Hypersensitivity to methotrexate (4)

5 WARNINGS AND PRECAUTIONS

- Organ system toxicity: Potential for serious toxicity. Only for use by physicians experienced in antimetabolite therapy (5.1).
- Effects on reproduction: May cause impairment of fertility, oligospermia and menstrual dysfunction (5.3, 8.3).
- Laboratory tests: Monitor complete blood counts, renal function and liver function tests (5.4).
- Risks from improper dosing: Mistaken daily use has led to fatal toxicity (5.5).
- Patients with impaired renal function, ascites, or pleural effusions: Elimination is reduced (5.6).
- Dizziness and fatigue: May impair ability to drive or operate machinery (5.7).

6 ADVERSE REACTIONS

Common adverse reactions are: nausea, abdominal pain, dyspepsia, stomatitis/mouth sores, rash, nasopharyngitis, diarrhea, liver function test abnormalities, vomiting, headache, bronchitis, thrombocytopenia, alopecia, leucopenia, pancytopenia, dizziness, photosensitivity, and “burning of skin lesions” (6).

To report SUSPECTED ADVERSE REACTIONS, contact Antares at 1-855-Otrexup (1-855-687-3987) or FDA at 1-800-FDA-1088 orwww.fda.gov/medwatch.

7 DRUG INTERACTIONS

- Aspirin, NSAIDs, and steroids: concomitant use may elevate and prolong serum methotrexate levels and cause increased toxicity (7.1).
- Proton pump inhibitors :concomitant use may elevate and prolong serum methotrexate levels and cause increased toxicity (7.2).

8 USE IN SPECIFIC POPULATIONS

- Pediatric use: Safety and efficacy of methotrexate, including Otrexup, have not been established in pediatric patients with psoriasis. Safety and efficacy of Otrexup have not been established in pediatric patients with malignancy (8.4).
- Geriatric use: Use caution in dose selection (8.5).
- Lactation: Advise women not to breastfeed (8.2).

FULL PRESCRIBING INFORMATION

WARNING: SEVERE TOXIC REACTIONS, INCLUDING EMBRYO-FETAL TOXICITY AND DEATH

Otrexupshould be used only by physicians whose knowledge and experience include the use of antimetabolite therapy. Because of the possibility of serious toxic reactions (which can be fatal), Otrexupshould be used only in patients with psoriasis or rheumatoid arthritis with severe, recalcitrant, disabling disease which is not adequately responsive to other forms of therapy. Deaths have been reported with the use of methotrexate in the treatment of malignancy, psoriasis, and rheumatoid arthritis. Patients should be closely monitored for bone marrow, liver, lung, skin, and kidney toxicities. Patients should be informed by their physician of the risks involved and be under a physician’s care throughout therapy [see Warnings and Precautions (5.1)].

1. Methotrexate can cause embryo-fetal toxicity, including fetal death.

Use is contraindicated during pregnancy. Verify the pregnancy status of females of reproductive potential prior to initiating therapy. Advise females and males of reproductive potential to use effective contraception during and after treatment with Otrexup [see Contraindications (4), Warnings and Precautions (5.2), and Use in Specific Populations (8.1, 8.3)].

2. Methotrexate elimination is reduced in patients with impaired renal functions, ascites, or pleural effusions. Such patients require especially careful monitoring for toxicity, and require dose reduction or, in some cases, discontinuation of Otrexupadministration [see Warnings and Precautions (5.6)] .

3. Unexpectedly severe (sometimes fatal) bone marrow suppression, aplastic anemia, and gastrointestinal toxicity have been reported with concomitant administration of methotrexate (usually in high dosage) along with somenonsteroidalanti-inflammatory drugs (NSAIDs) [see Warnings and Precautions (5.1) and Drug Interactions (7.1)].

4. Methotrexate causes hepatotoxicity, fibrosis and cirrhosis, but generally only after prolonged use. Acutely, liver enzyme elevations are frequently seen. These are usually transient and asymptomatic, and also do not appear predictive of subsequent hepatic disease. Liver biopsy after sustained use often shows histologic changes, and fibrosis and cirrhosis have been reported; these latter lesions may not be preceded by symptoms or abnormal liver function tests in the psoriasis population. For this reason, periodic liver biopsies are usually recommended for psoriatic patients who are underlong-termtreatment. Persistent abnormalities in liver function tests may precede appearance of fibrosis or cirrhosis in the rheumatoid arthritis population [see Warnings and Precautions (5.1)].

5. Methotrexate-induced lung disease, including acute or chronic interstitial pneumonitis, is a potentially dangerous lesion, which may occur acutely at any time during therapy and has been reported at low doses. It is not always fully reversible and fatalities have been reported. Pulmonary symptoms (especially a dry, nonproductive cough) may require interruption of treatment and careful investigation [see Warnings and Precautions (5.1)].

6. Diarrhea and ulcerative stomatitis require interruption of therapy: otherwise, hemorrhagic enteritis and death from intestinal perforation may occur [see Warnings and Precautions (5.1)].

7. Malignant lymphomas, which may regress following withdrawal of methotrexate, may occur in patients receiving low-dose methotrexate and, thus, may not require cytotoxic treatment. Discontinue Otrexupfirst and, if the lymphoma does not regress, appropriate treatment should be instituted [see Warnings and Precautions (5.8)] .

8. Like other cytotoxic drugs, methotrexate may induce “tumorlysissyndrome” in patients with rapidly growing tumors [see Warnings and Precautions (5.9)] .

9. Severe, occasionally fatal, skin reactions have been reported following single or multiple doses of methotrexate. Reactions have occurred within days of oral, intramuscular, intravenous, orintrathecalmethotrexate administration. Recovery has been reported with discontinuation of therapy [see Warnings and Precautions (5.1)] .

10. Potentially fatal opportunistic infections, especially Pneumocystisjirovecipneumonia, may occur with methotrexate therapy [see Warnings and Precautions (5.1)] .

11. Methotrexate given concomitantly with radiotherapy may increase the risk of soft tissue necrosis and osteonecrosis [see Warnings and Precautions (5.10)] .

1 INDICATIONS AND USAGE

1.1 Rheumatoid Arthritis including Polyarticular Juvenile Idiopathic Arthritis

Otrexup is indicated in the management of selected adults with severe, active rheumatoid arthritis (RA) (ACR criteria), or children with active polyarticular juvenile idiopathic arthritis (pJIA), who have had an insufficient therapeutic response to, or are intolerant of, an adequate trial of first-line therapy including full dose non-steroidal anti-inflammatory agents (NSAIDs).

1.2 Psoriasis

Otrexup is indicated in adults for the symptomatic control of severe, recalcitrant, disabling psoriasis that is not adequately responsive to other forms of therapy, but only when the diagnosis has been established, as by biopsy and/or after dermatologic consultation. It is important to ensure that a psoriasis “flare” is not due to an undiagnosed concomitant disease affecting immune responses.

1.3 Limitation of Use

Otrexup is not indicated for the treatment of neoplastic diseases.

2 DOSAGE AND ADMINISTRATION

2.1 Important Dosing Information

Otrexup is a single-dose auto-injector for once-weekly subcutaneous use only [see Warnings and Precautions (5.5)] . Administer Otrexup in the abdomen or the thigh. Otrexup is available in the following dosage strengths: 10, 12.5, 15, 17.5, 20, 22.5 and 25 mg. Use another formulation of methotrexate for alternative dosing in patients who require oral, intramuscular, intravenous, intra-arterial, or intrathecal dosing, doses less than 10 mg per week, doses more than 25 mg per week, high-dose regimens, or dose adjustments between the available doses.

2.2 Rheumatoid Arthritis including Polyarticular Juvenile Idiopathic Arthritis

Recommended starting dose of methotrexate:

Adult RA:7.5 mg once weekly.

pJIA:10 mg/m^2once weekly.

For patients switching from oral methotrexate to Otrexup, consider any differences in bioavailability between oral and subcutaneously administered methotrexate [see Clinical Pharmacology (12.3)] .

Dosages may be adjusted gradually to achieve an optimal response. Limited experience shows a significant increase in the incidence and severity of serious toxic reactions, especially bone marrow suppression, at doses greater than 20 mg/wk in adults. Although there is experience with doses up to 30 mg/m^2/wk in children, there are too few published data to assess how doses over 20 mg/m^2/wk might affect the risk of serious toxicity in children. Experience does suggest, however, that children receiving 20 to 30 mg/m^2/wk (0.65 to 1.0 mg/kg/wk) may have better absorption and fewer gastrointestinal side effects if methotrexate is administered either intramuscularly or subcutaneously.

Therapeutic response usually begins within 3 to 6 weeks and the patient may continue to improve for another 12 weeks or more.

The optimal duration of therapy is unknown. Limited data available from long-term studies in adults indicate that the initial clinical improvement is maintained for at least two years with continued therapy. When methotrexate is discontinued, the arthritis usually worsens within 3 to 6 weeks.

The patient should be fully informed of the risks involved and should be under constant supervision of the physician.Assessment of hematologic, hepatic, renal, and pulmonary function should be made by history, physical examination, and laboratory tests before beginning, periodically during, and before reinstituting Otrexup therapy [see Warnings and Precautions (5.4)] . Females of childbearing potential should not be started on Otrexup until pregnancy is excluded [see Contraindications (4) and Warnings and Precautions (5.2)]

All schedules should be continually tailored to the individual patient. An initial test dose may be given prior to the regular dosing schedule to detect any extreme sensitivity to adverse effects.

Maximal myelosuppression usually occurs in seven to ten days.

2.3 Psoriasis

Recommended starting dose of methotrexate:

Psoriasis:single weekly oral, intramuscular, subcutaneous, or intravenous doses of 10-25 mg.

For patients switching from oral methotrexate to Otrexup, consider any differences in bioavailability between oral and subcutaneously administered methotrexate [see Clinical Pharmacology (12.3)] .

Dosage may be gradually adjusted to achieve optimal clinical response; 30 mg/week should not ordinarily be exceeded. Once optimal clinical response has been achieved, the dosage should be reduced to the lowest possible amount of drug and to the longest possible rest period. The use of Otrexup may permit the return to conventional topical therapy, which should be encouraged.

2.4 Administration and Handling

Otrexup is an auto-injector intended for subcutaneous use under the guidance and supervision of a physician.

Patients may self-inject with Otrexup if a physician determines that it is appropriate, if they have received proper training in how to prepare and administer the correct dose, and if they receive medical follow-up, as necessary. A trainer device is available for training purposes.

Visually inspect Otrexup for particulate matter and discoloration prior to administration. Do not use Otrexup if the seal is broken.

Handle and dispose of Otrexup consistent with recommendations for handling and disposal of cytotoxic drugs^1.

2.5 Pregnancy testing

Verify the pregnancy status of females of reproductive potential prior to initiating treatment with Otrexup [see Use in Specific Populations (8.1, 8.3)] .

3 DOSAGE FORMS AND STRENGTHS

Otrexup is an injection available as an autoinjector that administers a single 0.4 mL dose of methotrexate solution in the following dosage strengths:

- 10 mg/0.4 mL methotrexate
- 12.5 mg/0.4 mL methotrexate
- 15 mg/0.4 mL methotrexate
- 17.5 mg/0.4 mL methotrexate
- 20 mg/0.4 mL methotrexate
- 22.5 mg/0.4 mL methotrexate
- 25 mg/0.4 mL methotrexate

4 CONTRAINDICATIONS

Otrexup is contraindicated in the following:

• Pregnancy

Otrexup can cause embryo-fetal toxicity and fetal death when administered during pregnancy [see Warnings and Precautions (5.2) and Use in Specific Populations (8.1)].

• Alcoholism or Liver Disease

Patients with alcoholism, alcoholic liver disease or other chronic liver disease [see Warnings and Precautions (5.1) ].

• Immunodeficiency Syndromes

Patients who have overt or laboratory evidence of immunodeficiency syndromes [ see Warnings and Precautions (5.1) ].

• Preexisting Blood Dyscrasias

Patients who have preexisting blood dyscrasias, such as bone marrow hypoplasia, leukopenia, thrombocytopenia, or significant anemia [see Warnings and Precautions (5.1)].

• Hypersensitivity

Patients with a known hypersensitivity to methotrexate. Severe hypersensitivity reactions have been observed with methotrexate use [see Warnings and Precautions (5.1) and Adverse Reactions (6.1and 6.2)].

5 WARNINGS AND PRECAUTIONS

5.1 Organ System Toxicity

Otrexup should be used only by physicians whose knowledge and experience include the use of antimetabolite therapy. Because of the possibility of serious toxic reactions (which can be fatal), Otrexup should be used only in patients with psoriasis or rheumatoid arthritis with severe, recalcitrant, disabling disease which is not adequately responsive to other forms of therapy.

Deaths have been reported with the use of methotrexate in the treatment of malignancy, psoriasis, and rheumatoid arthritis. Patients should be closely monitored for bone marrow, liver, lung and kidney toxicities.

Otrexup has the potential for serious toxicity. Toxic effects may be related in frequency and severity to dose or frequency of administration but have been seen at all doses. Because they can occur at any time during therapy, it is necessary to follow patients on Otrexup closely. Most adverse reactions are reversible if detected early. When such reactions do occur, the drug should be reduced in dosage or discontinued and appropriate corrective measures should be taken. If necessary, this could include the use of leucovorin calcium and/or acute, intermittent hemodialysis with a high-flux dialyzer [see Overdosage (10)] . If Otrexup therapy is reinstituted, it should be carried out with caution, with adequate consideration of further need for the drug and increased alertness as to possible recurrence of toxicity. The clinical pharmacology of methotrexate has not been well studied in older individuals. Due to diminished hepatic and renal function as well as decreased folate stores in this population, relatively low doses should be considered, and these patients should be closely monitored for early signs of toxicity [see Use in Specific Populations (8.5)].

Gastrointestinal:

Diarrhea and ulcerative stomatitis require interruption of therapy: otherwise, hemorrhagic enteritis and death from intestinal perforation may occur.

If vomiting, diarrhea, or stomatitis occur, which may result in dehydration, Otrexup should be discontinued until recovery occurs. Otrexup should be used with extreme caution in the presence of peptic ulcer disease or ulcerative colitis.

Unexpectedly severe (sometimes fatal) gastrointestinal toxicity has been reported with concomitant administration of methotrexate (usually in high dosage) along with some nonsteroidal anti-inflammatory drugs (NSAIDs) [see Drug Interactions (7.1)].

Hematologic:

Otrexup can suppress hematopoiesis and cause anemia, aplastic anemia, pancytopenia, leukopenia, neutropenia, and/or thrombocytopenia. In patients with preexisting hematopoietic impairment, Otrexup should be used with caution, if at all. In controlled clinical trials conducted with another formulation of methotrexate in rheumatoid arthritis (n=128), leukopenia (WBC <3000/mm^3) was seen in 2 patients, thrombocytopenia (platelets <100,000/mm^3) in 6 patients, and pancytopenia in 2 patients.

Otrexup should be stopped immediately if there is a significant drop in blood counts. Patients with profound granulocytopenia and fever should be evaluated immediately and usually require parenteral broad-spectrum antibiotic therapy.

Unexpectedly severe (sometimes fatal) bone marrow suppression and aplastic anemia have been reported with concomitant administration of methotrexate (usually in high dosage) along with some nonsteroidal anti-inflammatory drugs (NSAIDs) [see Drug Interactions (7.1)].

Hepatic:

Otrexup has the potential for acute (elevated transaminases) and chronic (fibrosis and cirrhosis) hepatotoxicity. Chronic toxicity is potentially fatal; it generally has occurred after prolonged use (generally two years or more) and after a total dose of at least 1.5 grams. In studies in psoriatic patients, hepatotoxicity appeared to be a function of total cumulative dose and appeared to be enhanced by alcoholism, obesity, diabetes and advanced age. An accurate incidence rate has not been determined; the rate of progression and reversibility of lesions is not known. Special caution is indicated in the presence of preexisting liver damage or impaired hepatic function.

In psoriasis, liver function tests, including serum albumin, should be performed periodically prior to dosing but are often normal in the face of developing fibrosis or cirrhosis. These lesions may be detectable only by biopsy. The usual recommendation is to obtain a liver biopsy at 1) pretherapy or shortly after initiation of therapy (2 to 4 months), 2) a total cumulative dose of 1.5 grams, and 3) after each additional 1.0 to 1.5 grams. Moderate fibrosis or any cirrhosis normally leads to discontinuation of the drug; mild fibrosis normally suggests a repeat biopsy in 6 months.

Milder histologic findings such as fatty change and low grade portal inflammation, are relatively common pretherapy. Although these mild changes are usually not a reason to avoid or discontinue Otrexup therapy, the drug should be used with caution.

In rheumatoid arthritis, age at first use of methotrexate and duration of therapy have been reported as risk factors for hepatotoxicity; other risk factors, similar to those observed in psoriasis, may be present in rheumatoid arthritis but have not been confirmed to date. Persistent abnormalities in liver function tests may precede appearance of fibrosis or cirrhosis in this population. There is a combined reported experience in 217 rheumatoid arthritis patients with liver biopsies both before and during treatment (after a cumulative dose of at least 1.5 g) and in 714 patients with a biopsy only during treatment. There are 64 (7%) cases of fibrosis and 1 (0.1%) case of cirrhosis. Of the 64 cases of fibrosis, 60 were deemed mild. The reticulin stain is more sensitive for early fibrosis and its use may increase these figures. It is unknown whether even longer use will increase these risks.

Liver function tests should be performed at baseline at 4 to 8 week intervals in patients receiving Otrexup for rheumatoid arthritis. Pretreatment liver biopsy should be performed for patients with a history of excessive alcohol consumption, persistently abnormal baseline liver function test values or chronic hepatitis B or C infection. During therapy, liver biopsy should be performed if there are persistent liver function test abnormalities or there is a decrease in serum albumin below the normal range (in the setting of well controlled rheumatoid arthritis).

If the results of a liver biopsy show mild changes (Roenigk, grades I, II, IIIa), Otrexup may be continued and the patient monitored as per recommendations listed above. Otrexup should be discontinued in any patient who displays persistently abnormal liver function tests and refuses liver biopsy or in any patient whose liver biopsy shows moderate to severe changes (Roenigk grade IIIb or IV).

Infection or Immunologic States:

Otrexup should be used with extreme caution in the presence of active infection, and is contraindicated in patients with overt or laboratory evidence of immunodeficiency syndromes.

Immunization may be ineffective when given during Otrexup therapy. Immunization with live virus vaccines is generally not recommended. There have been reports of disseminated vaccinia infections after smallpox immunizations in patients receiving methotrexate therapy. Hypogammaglobulinemia has been reported rarely.

Potentially fatal opportunistic infections, especially Pneumocystisjirovecipneumonia, may occur with Otrexup therapy. When a patient presents with pulmonary symptoms, the possibility of Pneumocystisjirovecipneumonia should be considered.

Neurologic:

There have been reports of leukoencephalopathy following intravenous administration of methotrexate to patients who have had craniospinal irradiation. Serious neurotoxicity, frequently manifested as generalized or focal seizures, has been reported with unexpectedly increased frequency among pediatric patients with acute lymphoblastic leukemia who were treated with intermediate-dose intravenous methotrexate (1 gm/m^2). Symptomatic patients were commonly noted to have leukoencephalopathy and/or microangiopathic calcifications on diagnostic imaging studies. Chronic leukoencephalopathy has also been reported in patients who received repeated doses of high-dose methotrexate with leucovorin rescue even without cranial irradiation.

Discontinuation of methotrexate does not always result in complete recovery. A transient acute neurologic syndrome has been observed in patients treated with high dose regimens. Manifestations of this stroke-like encephalopathy may include confusion, hemiparesis, transient blindness, seizures and coma. The exact cause is unknown. After the intrathecal use of methotrexate, the central nervous system toxicity which may occur can be classified as follows: acute chemical arachnoiditis manifested by such symptoms as headache, back pain, nuchal rigidity, and fever; sub-acute myelopathy characterized by paraparesis/paraplegia associated with involvement with one or more spinal nerve roots; chronic leukoencephalopathy manifested by confusion, irritability, somnolence, ataxia, dementia, seizures and coma. This condition can be progressive and even fatal.

Pulmonary:

Methotrexate-induced lung disease, including acute or chronic interstitial pneumonitis, is a potentially dangerous lesion, which may occur acutely at any time during therapy and has been reported at low doses. It is not always fully reversible and fatalities have been reported.

Pulmonary symptoms (especially a dry nonproductive cough) or a non-specific pneumonitis occurring during Otrexup therapy may be indicative of a potentially dangerous lesion and require interruption of treatment and careful investigation. Although clinically variable, the typical patient with methotrexate induced lung disease presents with fever, cough, dyspnea, hypoxemia, and an infiltrate on chest X-ray; infection (including pneumonia) needs to be excluded. This lesion can occur at all dosages.

Renal:

Otrexup may cause renal damage that may lead to acute renal failure. High doses of methotrexate used in the treatment of osteosarcoma may cause renal damage leading to acute renal failure. Nephrotoxicity is due primarily to the precipitation of methotrexate and 7- hydroxymethotrexate in the renal tubules. Close attention to renal function including adequate hydration, urine alkalinization and measurement of serum methotrexate and creatinine levels are essential for safe administration.

Skin:

Severe, occasionally fatal, dermatologic reactions, including toxic epidermal necrolysis, Stevens-Johnson syndrome, exfoliative dermatitis, skin necrosis, and erythema multiforme, have been reported in children and adults, within days of oral, intramuscular, intravenous, or intrathecal methotrexate administration. Reactions were noted after single or multiple low, intermediate, or high doses of methotrexate in patients with neoplastic and non-neoplastic diseases.

Lesions of psoriasis may be aggravated by concomitant exposure to ultraviolet radiation.

Radiation dermatitis and sunburn may be “recalled” by the use of methotrexate.

Other precautions:

Otrexup should be used with extreme caution in the presence of debility.

Methotrexate exits slowly from third space compartments (e.g., pleural effusions or ascites). This results in a prolonged terminal plasma half-life and unexpected toxicity. In patients with significant third space accumulations, it is advisable to evacuate the fluid before treatment and to monitor plasma methotrexate levels.

5.2 Embryo-Fetal Toxicity

Based on published reports and methotrexate’s mechanism of action, methotrexate can cause embryo-fetal toxicity and fetal death when administered to a pregnant woman. In pregnant women Otrexup is contraindicated. Verify pregnancy status in females of reproductive potential prior to initiating Otrexup.

Advise females of reproductive potential to use effective contraception during treatment with Otrexup and for 6 months after the final dose. Advise males of reproductive potential to use effective contraception during Otrexup treatment and for at least 3 months after the final dose [see Contraindications (4), Use in Specific Populations (8.1, 8.3), Clinical Pharmacology (12.1)].

5.3 Effects on Reproduction

Based on published reports, methotrexate can cause impairment of fertility, oligospermia, and menstrual dysfunction. It is not known if the infertility is reversible in affected patients. Discuss the risk of effects on reproduction with female and male patients of reproductive potential. [see Use in Specific Populations (8.3)].

5.4 Laboratory Tests

Patients undergoing Otrexup therapy should be closely monitored so that toxic effects are detected promptly. Baseline assessment should include a complete blood count with differential and platelet counts, hepatic enzymes, renal function tests and a chest X-ray.

During therapy, monitoring of these parameters is recommended: hematology at least monthly, renal function and liver function every 1 to 2 months [see Warnings and Precautions (5.1)].

During initial or changing doses, or during periods of increased risk of elevated methotrexate blood levels (e.g., dehydration), more frequent monitoring may also be indicated.

Liver Function Tests

Transient liver function test abnormalities are observed frequently after methotrexate administration and are usually not cause for modification of methotrexate therapy. Persistent liver function test abnormalities, and/or depression of serum albumin may be indicators of serious liver toxicity and require evaluation [see Warnings and Precautions (5.1)].

A relationship between abnormal liver function tests and fibrosis or cirrhosis of the liver has not been established for patients with psoriasis. Persistent abnormalities in liver function tests may precede appearance of fibrosis or cirrhosis in the rheumatoid arthritis population.

Pulmonary Function Tests

Pulmonary function tests may be useful if methotrexate-induced lung disease is suspected, especially if baseline measurements are available [see Warnings and Precautions (5.1)].

5.5 Risks from Improper Dosing

Both the physician and pharmacist should emphasize to the patient that Otrexup is administered weekly and that mistaken daily use has led to fatal toxicity [see Dosage and Administration (2)].

5.6 Patients with Impaired Renal Function, Ascites, or Pleural Effusions

Methotrexate elimination is reduced in patients with impaired renal function, ascites, or pleural effusions. Such patients require especially careful monitoring for toxicity and require dose reduction or, in some cases, discontinuation of Otrexup administration.

5.7 Dizziness and Fatigue

Adverse reactions, such as dizziness and fatigue, may affect the ability to drive or operate machinery.

5.8 Malignant Lymphomas

Non-Hodgkin’s lymphoma and other tumors have been reported in patients receiving low-dose oral methotrexate. However, there have been instances of malignant lymphoma arising during treatment with low-dose oral methotrexate, which have regressed completely following withdrawal of methotrexate, without requiring active anti-lymphoma treatment. Discontinue Otrexup first and, if the lymphoma does not regress, appropriate treatment should be instituted.

5.9 Tumor Lysis Syndrome

Like other cytotoxic drugs, methotrexate may induce "tumor lysis syndrome" in patients with rapidly growing tumors.

5.10 Concomitant Radiation Therapy

Methotrexate given concomitantly with radiotherapy may increase the risk of soft tissue necrosis and osteonecrosis.

6 ADVERSE REACTIONS

The following adverse reactions are discussed in more detail in other sections of the labeling.

- Organ System Toxicity [see Warnings and Precautions (5.1)]
- Embryo-Fetal Toxicity [see Warnings and Precautions (5.2)]
- Effects on Reproduction [see Warnings and Precautions (5.3)]
- Malignant Lymphomas [see Warnings and Precautions (5.8)]

The most frequently reported adverse reactions include ulcerative stomatitis, leukopenia, nausea, and abdominal distress. Other frequently reported adverse reactions are malaise, undue fatigue, chills and fever, dizziness and decreased resistance to infection.

6.1 Clinical Trials Experience

This section provides a summary of adverse reactions reported in subjects in clinical studies conducted with Otrexup as well as with methotrexate injection and oral methotrexate.

Because clinical trials are conducted under widely varying conditions, adverse reaction rates observed in the clinical trials of a drug cannot be directly compared to rates in the clinical trials of another drug, and may not reflect the rates observed in practice.

Rheumatoid Arthritis

The approximate incidences of methotrexate-attributed (i.e. placebo rate subtracted) adverse reactions in 12 to 18 week double-blind studies of patients (n=128) with rheumatoid arthritis treated with low-dose oral (7.5 to 15 mg/week) pulse methotrexate, are listed below. Virtually all of these patients were on concomitant nonsteroidal anti-inflammatory drugs and some were also taking low dosages of corticosteroids. Hepatic histology was not examined in these short-term studies.

Incidence greater than 10%: Elevated liver function tests 15%, nausea/vomiting 10%.

Incidence 3% to 10%: Stomatitis, thrombocytopenia (platelet count less than 100,000/mm^3).

Incidence 1% to 3%: Rash/pruritis/dermatitis, diarrhea, alopecia, leukopenia (WBC less than 3000/mm^3), pancytopenia, dizziness.

Two other controlled trials of patients (n=680) with Rheumatoid Arthritis on 7.5 mg to 15 mg/wk oral doses showed an incidence of interstitial pneumonitis of 1%.

Other less common reactions included decreased hematocrit, headache, upper respiratory infection, anorexia, arthralgias, chest pain, coughing, dysuria, eye discomfort, epistaxis, fever, infection, sweating, tinnitus, and vaginal discharge.

Polyarticular Juvenile Idiopathic Arthritis

The approximate incidences of adverse reactions reported in pediatric patients with pJIA treated with oral, weekly doses of methotrexate (5 to 20 mg/m^2/wk or 0.1 to 0.65 mg/kg/wk) were as follows (virtually all patients were receiving concomitant nonsteroidal anti-inflammatory drugs, and some also were taking low doses of corticosteroids): elevated liver function tests, 14%; gastrointestinal reactions (e.g., nausea, vomiting, diarrhea), 11%; stomatitis, 2%; leukopenia, 2%; headache, 1.2%; alopecia, 0.5%; dizziness, 0.2%; and rash, 0.2%. Although there is experience with dosing up to 30 mg/m^2/wk in pJIA, the published data for doses above 20 mg/m^2/wk are too limited to provide reliable estimates of adverse reaction rates.

Psoriasis

There are two literature reports (Roenigk, 1969, and Nyfors, 1978) describing large series (n=204, 248) of psoriasis patients treated with methotrexate. Dosages ranged up to 25 mg per week and treatment was administered for up to four years. With the exception of alopecia, photosensitivity, and “burning of skin lesions” (each 3% to 10%), the adverse reaction rates in these reports were very similar to those in the rheumatoid arthritis studies. Rarely, painful plaque erosions may appear (Pearce, HP and Wilson, BB: Am Acad Dermatol 35: 835-838, 1996).

6.2 Other Adverse Reactions

Other adverse reactions that have been reported with methotrexate in oncology, RA, pJIA, and psoriasis patients are listed below by organ system.

Alimentary System:gingivitis, pharyngitis, stomatitis, anorexia, nausea, vomiting, diarrhea, hematemesis, melena, gastrointestinal ulceration and bleeding, enteritis, pancreatitis.

Blood and Lymphatic System Disorders:suppressed hematopoiesis, anemia, aplastic anemia, pancytopenia, leukopenia, neutropenia, thrombocytopenia, agranulocytosis, eosinophilia, lymphadenopathy and lymphoproliferative disorders (including reversible). Hypogammaglobulinemia has been reported rarely.

Cardiovascular:pericarditis, pericardial effusion, hypotension, and thromboembolic events (including arterial thrombosis, cerebral thrombosis, deep vein thrombosis, retinal vein thrombosis, thrombophlebitis, and pulmonary embolus).

Central Nervous System:headaches, drowsiness, blurred vision, transient blindness, speech impairment including dysarthria and aphasia, hemiparesis, paresis and convulsions have also occurred following administration of methotrexate. Following low doses, there have been occasional reports of transient subtle cognitive dysfunction, mood alteration or unusual cranial sensations, leukoencephalopathy, or encephalopathy.

Hepatobiliary Disorders:hepatotoxicity, acute hepatitis, chronic fibrosis and cirrhosis, hepatic failure, decrease in serum albumin, liver enzyme elevations.

Infection:There have been case reports of sometimes fatal opportunistic infections in patients receiving methotrexate therapy for neoplastic and non-neoplastic diseases. Pneumocystisjirovecipneumonia was the most common opportunistic infection. There have also been reports of infections, pneumonia, Cytomegalovirus infection, including cytomegaloviral pneumonia, sepsis, fatal sepsis, nocardiosis; histoplasmosis, cryptococcosis, Herpes zoster, Herpes simplexhepatitis, and disseminated Herpes simplex.

Musculoskeletal System:stress fracture.

Ophthalmic:conjunctivitis, serious visual changes of unknown etiology.

Pulmonary System:respiratory fibrosis, respiratory failure, alveolitis, interstitial pneumonitis deaths have been reported, and chronic interstitial obstructive pulmonary disease has occasionally occurred.

Skin:erythematous rashes, pruritus, urticaria, photosensitivity, pigmentary changes, alopecia, ecchymosis, telangiectasia, acne, furunculosis, erythema multiforme, toxic epidermal necrolysis, Stevens-Johnson syndrome, skin necrosis, skin ulceration and exfoliative dermatitis.

Urogenital System:severe nephropathy or renal failure, azotemia, cystitis, hematuria, proteinuria; defective oogenesis or spermatogenesis, transient oligospermia, menstrual dysfunction, vaginal discharge, and gynecomastia; infertility, abortion, fetal death, fetal defects.

Other rarer reactions related to or attributed to the use of methotrexate such as nodulosis, vasculitis, arthralgia/myalgia, loss of libido/ impotence, diabetes, osteoporosis, sudden death, lymphoma, including reversible lymphomas, tumor lysis syndrome, soft tissue necrosis and osteonecrosis. Anaphylactoid reactions have been reported.

7 DRUG INTERACTIONS

7.1 Aspirin, Nonsteroidal Anti-Inflammatory Drugs, and Steroids

Nonsteroidal anti-inflammatory drugs (NSAIDs) should not be administered prior to or concomitantly with the high doses of methotrexate, such as used in the treatment of osteosarcoma. Concomitant administration of some NSAIDs with high dose methotrexate therapy has been reported to elevate and prolong serum methotrexate levels, resulting in deaths from severe hematologic and gastrointestinal toxicity [see Warnings and Precautions (5.1)].

Caution should be used when NSAIDs and salicylates are administered concomitantly with lower doses of methotrexate, including Otrexup. These drugs have been reported to reduce the tubular secretion of methotrexate in an animal model and may enhance its toxicity.

Despite the potential interactions, studies of methotrexate in patients with rheumatoid arthritis have usually included concurrent use of constant dosage regimens of NSAIDs, without apparent problems. It should be appreciated, however, that the doses used in rheumatoid arthritis (7.5 to 15 mg/week) are somewhat lower than those used in psoriasis and that larger doses could lead to unexpected toxicity. Aspirin, NSAIDs, and/or low dose steroids may be continued, although the possibility of increased toxicity with concomitant use of NSAIDs including salicylates has not been fully explored. Steroids may be reduced gradually in patients who respond to methotrexate.

7.2 Proton Pump Inhibitors (PPIs)

Use caution if high-dose methotrexate is administered to patients receiving proton pump inhibitor (PPI) therapy. Case reports and published population pharmacokinetic studies suggest that concomitant use of some PPIs, such as omeprazole, esomeprazole, and pantoprazole, with methotrexate (primarily at high dose), may elevate and prolong serum levels of methotrexate and/or its metabolite hydroxymethotrexate, possibly leading to methotrexate toxicities. In two of these cases, delayed methotrexate elimination was observed when high-dose methotrexate was co-administered with PPIs, but was not observed when methotrexate was co-administered with ranitidine. However, no formal drug interaction studies of methotrexate with ranitidine have been conducted.

7.3 Oral Antibiotics

Oral antibiotics such as tetracycline, chloramphenicol, and nonabsorbable broad spectrum antibiotics, may decrease intestinal absorption of methotrexate or interfere with the enterohepatic circulation by inhibiting bowel flora and suppressing metabolism of the drug by bacteria.

Penicillins may reduce the renal clearance of methotrexate; increased serum concentrations of methotrexate with concomitant hematologic and gastrointestinal toxicity have been observed with high and low dose methotrexate. Use of Otrexup with penicillins should be carefully monitored.

Trimethoprim/sulfamethoxazole has been reported rarely to increase bone marrow suppression in patients receiving methotrexate, probably by decreased tubular secretion and/or an additive antifolate effect.

7.4 Hepatotoxins

The potential for increased hepatotoxicity when methotrexate is administered with other hepatotoxic agents has not been evaluated. However, hepatotoxicity has been reported in such cases. Therefore, patients receiving concomitant therapy with Otrexup and other potential hepatotoxins (e.g., azathioprine, retinoids, and sulfasalazine) should be closely monitored for possible increased risk of hepatotoxicity.

7.5 Theophylline

Methotrexate may decrease the clearance of theophylline; theophylline levels should be monitored when used concurrently with Otrexup.

7.6 Folic Acid and Antifolates

Vitamin preparations containing folic acid or its derivatives may decrease responses to systemically administered methotrexate. Preliminary animal and human studies have shown that small quantities of intravenously administered leucovorin enter the CSF primarily as 5-methyltetrahydrofolate and, in humans, remain 1 to 3 orders of magnitude lower than the usual methotrexate concentrations following intrathecal administration. However, high doses of leucovorin may reduce the efficacy of intrathecally administered methotrexate. Folate deficiency states may increase methotrexate toxicity.

Trimethoprim/sulfamethoxazole has been reported rarely to increase bone marrow suppression in patients receiving methotrexate, probably by decreased tubular secretion and/or an additive antifolate effect.

7.7 Mercaptopurine

Methotrexate increases the plasma levels of mercaptopurine. The combination of Otrexup and mercaptopurine may therefore require dose adjustment.

7.8 Nitrous Oxide

The use of nitrous oxide anesthesia potentiates the effect of methotrexate on folate dependent metabolic pathways, resulting in the potential for increased toxicity. Avoid concomitant nitrous oxide anesthesia in patients receiving methotrexate.

7.9 Other Drugs

Methotrexate is partially bound to serum albumin, and toxicity may be increased because of displacement by certain drugs, such as salicylates, phenylbutazone, phenytoin, and sulfonamides.

Renal tubular transport is also diminished by probenecid; use of Otrexup with this drug should be carefully monitored.

Combined use of methotrexate with gold, penicillamine, hydroxychloroquine, sulfasalazine, or cytotoxic agents, has not been studied and may increase the incidence of adverse effects.

8 USE IN SPECIFIC POPULATIONS

8.1 Pregnancy

Risk Summary

Based on published reports and methotrexate’s mechanism of action, methotrexate can cause embryo-fetal toxicity and fetal death when administered to a pregnant woman [see Data and Clinical Pharmacology (12.1)] . In pregnant women with non-malignant disease, Otrexup is contraindicated. Consider the benefits and risks of Otrexup and risks to the fetus when prescribing Otrexup to a pregnant patient. There are no animal data that meet current standards for nonclinical developmental toxicity studies.

The estimated background risk of major birth defects and miscarriage for the indicated populations are unknown. All pregnancies have a background risk of birth defect, loss, or other adverse outcomes. In the U.S. general population, the estimated background risk of major birth defects and miscarriage in clinically recognized pregnancies is 2-4% and 15-20%, respectively.

Data

Human Data

Published data from cases, literature reviews, and observational studies report that methotrexate exposure during pregnancy is associated with an increased risk of embryo-fetal toxicity and fetal death. Methotrexate exposure during the first trimester of pregnancy is associated with an increased incidence of spontaneous abortions and multiple adverse developmental outcomes, including skull anomalies, facial dysmorphism, central nervous system abnormalities, limb abnormalities, and sometimes cardiac anomalies and intellectual impairment. Adverse outcomes associated with exposure during second and third trimesters of pregnancy include intrauterine growth restriction and functional abnormalities. Because methotrexate is widely distributed and persists in the body for a prolonged period, there is a potential risk to the fetus from preconception methotrexate exposure.

A prospective multicenter study evaluated pregnancy outcomes in women taking methotrexate less than or equal to 30 mg/week after conception. The rate of miscarriage in pregnant women exposed to methotrexate was 42.5% (95% confidence interval [95% CI] 29.2-58.7), which was higher than in unexposed patients with autoimmune disease (22.5%, 95% CI 16.8-29.7) and unexposed patients with non-autoimmune disease (17.3%, 95% CI 13-22.8). Of the live births, the rate of major birth defects in pregnant women exposed to methotrexate after conception was higher than in unexposed patients with autoimmune disease (adjusted odds ratio (OR) 1.8 [95% CI 0.6-5.7]) and unexposed patients with non-autoimmune disease (adjusted OR 3.1 [95% CI 1.03-9.5]). Major birth defects associated with pregnancies exposed to methotrexate after conception were not always consistent with methotrexate-associated adverse developmental outcomes.

8.2 Lactation

Risk Summary

Limited published literature report the presence of methotrexate in human milk in low amounts following oral methotrexate administration, with the highest breast milk to plasma concentration ratio reported to be 0.08:1. No information is available on the effects of methotrexate on a breastfed infant or on milk production. Because of the potential for serious adverse reactions including myelosuppression, from methotrexate in breastfed infants, advise women not to breastfeed during treatment with Otrexup and for one week after the final dose.

8.3 Females and Males of Reproductive Potential

Pregnancy Testing

Verify the pregnancy status of females of reproductive potential prior to initiating Otrexup.

Contraception

Females

Otrexup can cause fetal harm when administered to a pregnant woman [see Use in Specific Populations (8.1)] .

Advise females of reproductive potential to use effective contraception during and for 6 months after the final dose of Otrexup.

Males

Methotrexate can cause chromosomal damage to sperm cells. Advise males with female partners of reproductive potential to use effective contraception during and for at least 3 months after the final dose of Otrexup.

Infertility

Females

Based on published reports of female infertility after treatment with methotrexate, advise females of reproductive potential that Otrexup can cause impairment of fertility and menstrual dysfunction during and after cessation of therapy. It is not known if the infertility may be reversed in all affected females.

Males

Based on published reports of male infertility after treatment with methotrexate, advise males of reproductive potential that Otrexup can cause oligospermia or infertility during and after cessation of therapy. It is not known if the infertility may be reversed in all affected males.

8.4 Pediatric Use

The safety and effectiveness of methotrexate, including Otrexup, have not been established in pediatric patients with psoriasis.

The safety and effectiveness of Otrexup have not been established in pediatric patients with neoplastic diseases.

The safety and effectiveness of methotrexate have been established in pediatric patients with polyarticular juvenile idiopathic arthritis [see Clinical Studies (14.2)] .

Published clinical studies evaluating the use of methotrexate in children and adolescents (i.e., patients 2 to 16 years of age) with pJIA demonstrated safety comparable to that observed in adults with rheumatoid arthritis [ see Adverse Reactions (6.1) ].

Otrexup does not contain a preservative. However, methotrexate injectable formulations containing the preservative benzyl alcohol are not recommended for use in neonates. There have been reports of fatal ‘gasping syndrome’ in neonates (children less than one month of age) following the administrations of intravenous solutions containing the preservative benzyl alcohol. Symptoms include a striking onset of gasping respiration, hypotension, bradycardia, and cardiovascular collapse.

Serious neurotoxicity, frequently manifested as generalized or focal seizures, has been reported with unexpectedly increased frequency among pediatric patients with acute lymphoblastic leukemia who were treated with intermediate-dose intravenous methotrexate (1 gm/m^2) [see Warnings and Precautions (5.1)] .

8.5 Geriatric Use

Clinical studies of methotrexate did not include sufficient numbers of subjects age 65 and over to determine whether they respond differently from younger subjects. In general, dose selection for an elderly patient should be cautious reflecting the greater frequency of decreased hepatic and renal function, decreased folate stores, concomitant disease or other drug therapy (i.e., that interfere with renal function, methotrexate or folate metabolism) in this population [see Warnings and Precautions (5.1), Drug Interactions (7.7) and Use in Specific Populations (8.6)]. Since decline in renal function may be associated with increases in adverse reactions and serum creatinine measurements may over estimate renal function in the elderly, more accurate methods (i.e., creatinine clearance) should be considered. Serum methotrexate levels may also be helpful. Elderly patients should be closely monitored for early signs of hepatic, bone marrow and renal toxicity. In chronic use situations, certain toxicities may be reduced by folate supplementation. Post-marketing experience suggests that the occurrence of bone marrow suppression, thrombocytopenia, and pneumonitis may increase with age [see Warnings and Precautions (5.1)].

8.6 Renal Impairment

Methotrexate elimination is reduced in patients with impaired renal function. Such patients require especially careful monitoring for toxicity and require dose reduction or, in some cases, discontinuation of Otrexup administration.

8.7 Hepatic Impairment

The effect of hepatic impairment on methotrexate pharmacokinetics has not been studied. Otrexup is contraindicated in patients with alcoholic liver disease or other chronic liver disease. Patients with obesity, diabetes, hepatic fibrosis or steatohepatitis are at increased risk for hepatic injury and fibrosis secondary to methotrexate, and should be monitored closely [see Warnings and Precautions (5.1)] .

10 OVERDOSAGE

Leucovorin is indicated to diminish the toxicity and counteract the effect of inadvertently administered overdosages of methotrexate. Leucovorin administration should begin as promptly as possible. As the time interval between methotrexate administration and leucovorin initiation increases, the effectiveness of leucovorin in counteracting toxicity decreases. Monitoring of the serum methotrexate concentration is essential in determining the optimal dose and duration of treatment with leucovorin.

In cases of massive overdosage, hydration and urinary alkalinization may be necessary to prevent the precipitation of methotrexate and/or its metabolites in the renal tubules. Generally speaking, neither hemodialysis nor peritoneal dialysis has been shown to improve methotrexate elimination. However, effective clearance of methotrexate has been reported with acute, intermittent hemodialysis using a high-flux dialyzer (Wall, SM et al: Am J Kidney Dis28 (6): 846-854, 1996).

Accidental intrathecal overdosage may require intensive systemic support, high-dose systemic leucovorin, alkaline diuresis and rapid CSF drainage and ventriculolumbar perfusion.

In postmarketing experience, overdose with methotrexate has generally occurred with oral and intrathecal administration, although intravenous and intramuscular overdose have also been reported.

Reports of oral overdose often indicate accidental daily administration instead of weekly (single or divided doses). Symptoms commonly reported following oral overdose include those symptoms and signs reported at pharmacologic doses, particularly hematologic and gastrointestinal reaction. For example, leukopenia, thrombocytopenia, anemia, pancytopenia, bone marrow suppression, mucositis, stomatitis, oral ulceration, nausea, vomiting, gastrointestinal ulceration, gastrointestinal bleeding. In some cases, no symptoms were reported.

There have been reports of death following overdose. In these cases, events such as sepsis or septic shock, renal failure, and aplastic anemia were also reported.

Symptoms of intrathecal overdose are generally central nervous system (CNS) symptoms, including headache, nausea and vomiting, seizure or convulsion, and acute toxic encephalopathy. In some cases, no symptoms were reported. There have been reports of death following intrathecal overdose. In these cases, cerebellar herniation associated with increased intracranial pressure, and acute toxic encephalopathy have also been reported.

There are published case reports of intravenous and intrathecal carboxypeptidase G2 treatment to hasten clearance of methotrexate in cases of overdose.

11 DESCRIPTION

Otrexup contains methotrexate, a folate analog metabolic inhibitor.

Chemically, methotrexate is [N-[4-[[(2,4-diamino-6-pteridinyl)methyl]methylamino]benzoyl]-Lglutamic acid. The structural formula is:

C20H22N8O5M.W.= 454.45

Otrexup contains methotrexate in a sterile, preservative-free, unbuffered solution with a 27 gauge ½ inch needle for a single subcutaneous injection. Otrexup solution is yellow in color.

Inactive ingredients include sodium chloride and water for injection, USP. The amounts of sodium chloride vary with the amount of methotrexate.

Amount of methotrexate (mg) per 0.4 mL | 10 | 12.5 | 15 | 17.5 | 20 | 22.5 | 25
Amount of sodium chloride (mg) per 0.4 mL | 1.96 | 2.04 | 1.60 | 1.48 | 1.28 | 0.92 | 0.56

Hydrochloric acid and additional sodium hydroxide may have been added, if necessary, to adjust the pH to 8.0.

12 CLINICAL PHARMACOLOGY

12.1 Mechanism of Action

Methotrexate inhibits dihydrofolic acid reductase. Dihydrofolates must be reduced to tetrahydrofolates by this enzyme before they can be utilized as carriers of one-carbon groups in the synthesis of purine nucleotides and thymidylate. Therefore, methotrexate interferes with DNA synthesis, repair, and cellular replication. Actively proliferating tissues such as malignant cells, bone marrow, fetal cells, buccal and intestinal mucosa, and cells of the urinary bladder are in general more sensitive to this effect of methotrexate.

The mechanism of action in rheumatoid arthritis is unknown; it may affect immune function.

12.2 Pharmacodynamics

Two reports describe in vitromethotrexate inhibition of DNA precursor uptake by stimulated mononuclear cells, and another describes in animal polyarthritis partial correction by methotrexate of spleen cell hyporesponsiveness and suppressed IL 2 production. Other laboratories, however, have been unable to demonstrate similar effects. Clarification of methotrexate’s effect on immune activity and its relation to rheumatoid immunopathogenesis await further studies.

In psoriasis, the rate of production of epithelial cells in the skin is greatly increased over normal skin. This differential in proliferation rates is the basis for the use of methotrexate to control the psoriatic process.

Methotrexate in high doses, followed by leucovorin rescue, is used as a part of the treatment of patients with non-metastatic osteosarcoma. The original rationale for high dose methotrexate therapy was based on the concept of selective rescue of normal tissues by leucovorin. More recent evidence suggests that high dose methotrexate may also overcome methotrexate resistance caused by impaired active transport, decreased affinity of dihydrofolic acid reductase for methotrexate, increased levels of dihydrofolic acid reductase resulting from gene amplification, or decreased polyglutamation of methotrexate. The actual mechanism of action is unknown.

12.3 Pharmacokinetics

Absorption

In adults, oral absorption appears to be dose dependent. Peak serum levels are reached within one to two hours. At doses of 30 mg/m^2or less, methotrexate is generally well absorbed with a mean bioavailability of about 60%. The absorption of doses greater than 80 mg/m^2is significantly less, possibly due to a saturation effect.

In relative bioavailability studies in rheumatoid arthritis patients, systemic exposure of methotrexate was found to be similar between Otrexup and intramuscular or subcutaneous administration of methotrexate injection at the same doses, however systemic exposure of methotrexate was higher with Otrexup as compared to oral administration of methotrexate at the same dose. Bioavailability following oral dosing showed a plateau effect at doses of 15 mg and greater. The systemic exposure of methotrexate from Otrexup at doses of 10, 15, 20, and 25 mg was higher than that of oral methotrexate by 17, 13, 31, and 36%, respectively. Methotrexate systemic absorption from Otrexup was similar when administered into the abdomen or thigh.

In leukemic pediatric patients, oral absorption of methotrexate also appears to be dose dependent and has been reported to vary widely (23% to 95%). A twenty fold difference between highest and lowest peak levels (Cmax: 0.11 to 2.3 micromolar after a 20 mg/m^2dose) has been reported.

Significant interindividual variability has also been noted in time to peak concentration (Tmax: 0.67 to 4 hrs after a 15 mg/m^2dose) and fraction of dose absorbed. The absorption of doses greater than 40 mg/m^2has been reported to be significantly less than that of lower doses. Food has been shown to delay absorption and reduce peak concentration. Methotrexate is generally completely absorbed from parenteral routes of injection. After intramuscular injection, peak serum concentrations occur in 30 to 60 minutes. As in leukemic pediatric patients, a wide interindividual variability in the plasma concentrations of methotrexate has been reported in pediatric patients with JIA. Following oral administration of methotrexate in doses of 6.4 to 11.2 mg/m^2/week in pediatric patients with JIA, mean serum concentrations were 0.59 micromolar (range, 0.03 to 1.40) at 1 hour, 0.44 micromolar (range, 0.01 to 1.00) at 2 hours, and 0.29 micromolar (range, 0.06 to 0.58) at 3 hours.

Distribution

After intravenous administration, the initial volume of distribution is approximately 0.18 L/kg (18% of body weight) and steady-state volume of distribution is approximately 0.4 to 0.8 L/kg (40 to 80% of body weight). Methotrexate competes with reduced folates for active transport across cell membranes by means of a single carrier-mediated active transport process. At serum concentrations greater than 100 micromolar, passive diffusion becomes a major pathway by which effective intracellular concentrations can be achieved. Methotrexate in serum is approximately 50% protein bound. Laboratory studies demonstrate that it may be displaced from plasma albumin by various compounds including sulfonamides, salicylates, tetracyclines, chloramphenicol, and phenytoin.

Methotrexate does not penetrate the blood-cerebrospinal fluid barrier in therapeutic amounts when given orally or parenterally. High CSF concentrations of the drug may be attained by intrathecal administration of other parenteral forms of methotrexate.

In dogs, synovial fluid concentrations after oral dosing were higher in inflamed than uninflamed joints. Although salicylates did not interfere with this penetration, prior prednisone treatment reduced penetration into inflamed joints to the level of normal joints.

Metabolism

After absorption, methotrexate undergoes hepatic and intracellular metabolism to polyglutamated forms which can be converted back to methotrexate by hydrolase enzymes. These polyglutamates act as inhibitors of dihydrofolate reductase and thymidylate synthetase. Small amounts of methotrexate polyglutamates may remain in tissues for extended periods. The retention and prolonged drug action of these active metabolites vary among different cells, tissues and tumors. A small amount of metabolism to 7-hydroxymethotrexate may occur at doses commonly prescribed. Accumulation of this metabolite may become significant at the high doses used in osteogenic sarcoma. The aqueous solubility of 7-hydroxymethotrexate is 3 to 5 fold lower than the parent compound. Methotrexate is partially metabolized by intestinal flora after oral administration.

Half-Life

The terminal half-life reported for methotrexate is approximately three to ten hours for patients receiving treatment for psoriasis, or rheumatoid arthritis or low dose antineoplastic therapy (less than 30 mg/m^2). For patients receiving high doses of methotrexate, the terminal half-life is eight to 15 hours.

In pediatric patients receiving methotrexate for acute lymphocytic leukemia (6.3 to 30 mg/m^2), or for JIA (3.75 to 26.2 mg/m^2), the terminal half-life has been reported to range from 0.7 to 5.8 hours or 0.9 to 2.3 hours, respectively.

Excretion

Renal excretion is the primary route of elimination and is dependent upon dosage and route of administration. With IV administration, 80% to 90% of the administered dose is excreted unchanged in the urine within 24 hours. There is limited biliary excretion amounting to 10% or less of the administered dose. Enterohepatic recirculation of methotrexate has been proposed.

Renal excretion occurs by glomerular filtration and active tubular secretion. Nonlinear elimination due to saturation of renal tubular reabsorption has been observed in psoriatic patients at doses between 7.5 and 30 mg. Impaired renal function, as well as concurrent use of drugs such as weak organic acids that also undergo tubular secretion, can markedly increase methotrexate serum levels.

Excellent correlation has been reported between methotrexate clearance and endogenous creatinine clearance. Methotrexate clearance rates vary widely and are generally decreased at higher doses. Delayed drug clearance has been identified as one of the major factors responsible for methotrexate toxicity. It has been postulated that the toxicity of methotrexate for normal tissues is more dependent upon the duration of exposure to the drug rather than the peak level achieved. When a patient has delayed drug elimination due to compromised renal function, a third space effusion, or other causes, methotrexate serum concentrations may remain elevated for prolonged periods.

When other forms of parenteral methotrexate are administered during cancer chemotherapy, the potential for toxicity from high dose regimens or delayed excretion is reduced by the administration of leucovorin calcium during the final phase of methotrexate plasma elimination.

Pharmacokinetic monitoring of methotrexate serum concentrations may help identify those patients at high risk for methotrexate toxicity and aid in proper adjustments of leucovorin dosing.

13 NONCLINICAL TOXICOLOGY

13.1 Carcinogenesis, Mutagenesis, Impairment of Fertility

Methotrexate has been evaluated in a number of animal studies for carcinogenic potential with inconclusive results. Although there is evidence that methotrexate causes chromosomal damage to animal somatic cells and human bone marrow cells, the clinical significance remains uncertain.

Data are available regarding the risks for pregnancy and for fertility in humans [see Use in Specific Populations (8.1and 8.3)].

14 CLINICAL STUDIES

14.1 Rheumatoid Arthritis

Clinical trials in patients with rheumatoid arthritis were performed using other formulations of methotrexate.

In patients with rheumatoid arthritis, effects of methotrexate on articular swelling and tenderness can be seen as early as 3 to 6 weeks.

Most studies of methotrexate in patients with rheumatoid arthritis are relatively short term (3 to 6 months). Limited data from long-term studies indicate that an initial clinical improvement is maintained for at least two years with continued therapy.

14.2 Polyarticular Juvenile Idiopathic Arthritis

Clinical trials in patients with polyarticular juvenile idiopathic arthritis were performed using other formulations of methotrexate.

In a 6-month double-blind, placebo-controlled trial of 127 pediatric patients with pJIA (mean age, 10.1 years; age range, 2.5 to 18 years; mean duration of disease, 5.1 years) on background nonsteroidal anti-inflammatory drugs and/or prednisone, methotrexate given weekly at an oral dose of 10 mg/m^2provided significant clinical improvement compared to placebo as measured by either the physician’s global assessment, or by a patient composite (25% reduction in the articular-severity score plus improvement in parent and physician global assessments of disease activity). Over two-thirds of the patients in this trial had polyarticular-course JIA, and the numerically greatest response was seen in this subgroup treated with 10 mg/m^2/wk methotrexate.

The overwhelming majority of the remaining patients had systemic-course JIA. All patients were unresponsive to NSAIDs; approximately one-third were using low dose corticosteroids.

Weekly methotrexate at a dose of 5 mg/m^2was not significantly more effective than placebo in this trial.

15 REFERENCES

1. “Hazardous Drugs”. OSHA. http://www.osha.gov/SLTC/hazardousdrugs/index.html

16 HOW SUPPLIED/STORAGE AND HANDLING

Otrexup contains methotrexate in a preservative-free sterile solution for a single subcutaneous injection. Otrexup is available in the following strengths and configurations.

Otrexup (methotrexate) injection 10 mg/0.4 mL

- Carton of 1 NDC 54436-010-01
- Carton of 4 NDC 54436-010-04
  - Otrexup NDC 54436-010-02

Otrexup (methotrexate) injection 12.5 mg/0.4 mL

- Carton of 1 NDC 54436-012-01
- Carton of 4 NDC 54436-012-04
  - Otrexup NDC 54436-012-02

Otrexup (methotrexate) injection 15 mg/0.4 mL

- Carton of 1 NDC 54436-015-01
- Carton of 4 NDC 54436-015-04
  - Otrexup NDC 54436-015-02

Otrexup (methotrexate) injection 17.5 mg/0.4 mL

- Carton of 1 NDC 54436-017-01
- Carton of 4 NDC 54436-017-04
  - Otrexup NDC 54436-017-02

Otrexup (methotrexate) injection 20 mg/0.4 mL

- Carton of 1 NDC 54436-020-01
- Carton of 4 NDC 54436-020-04
  - Otrexup NDC 54436-020-02

Otrexup (methotrexate) injection 22.5 mg/0.4 mL

- Carton of 1 NDC 54436-022-01
- Carton of 4 NDC 54436-022-04
  - Otrexup NDC 54436-022-02

Otrexup (methotrexate) injection 25 mg/0.4 mL

- Carton of 1 NDC 54436-025-01
- Carton of 4 NDC 54436-025-04
  - Otrexup NDC 54436-025-02

Store at controlled room temperature, 25°C (77°F); excursions permitted to 15° to 30°C (59° to 86°F). PROTECT FROM LIGHT.

Handling and Disposal

Handle and dispose of Otrexup consistent with recommendations for handling and disposal of cytotoxic drugs.^1

17 PATIENT COUNSELING INFORMATION

See FDA-approved patient labeling (Patient Informationand Instructions for Use)

Risk of Organ Toxicity

Inform patients of the risks of organ toxicity, including gastrointestinal, hematologic, hepatic, infections, neurologic, pulmonary, renal and skin as well as possible signs and symptoms for which they should contact their healthcare provider. Advise patients of the need for close follow-up, including periodic laboratory tests to monitor toxicity [see Warnings and Precautions (5.1and 5.4)] .

Importance of Proper Dosing and Administration

Both the physician and pharmacist should emphasize to the patient that the recommended dose is taken weekly and that mistaken daily use of the recommended dose has led to fatal toxicity [see Dosing and Administration (2)] .

Otrexup is intended for use under the guidance and supervision of a physician. Patients should not self-administer until they receive training from a healthcare professional. The patient’s or caregiver’s ability to administer Otrexup should be assessed. A trainer device is available for training purposes.

Patients should be instructed to use administration sites on the abdomen or the thigh. Administration should not be made within 2 inches of the navel. Instruct patients not to administer Otrexup to the arms or any other areas of the body, as delineated in the Otrexup Instructions for Use [see Instructions for Use] .

Embryo-Fetal Toxicity

- Advise females of reproductive potential that Otrexup can cause fetal harm and is contraindicated in pregnancy. Advise women of childbearing potential that Otrexup should not be started until pregnancy is excluded. Women should be fully counseled on the serious risk to the fetus should they become pregnant while undergoing treatment. Inform patients to contact their physician if they suspect that they are pregnant [see Boxed Warning, Contraindications (4), Warnings and Precautions (5.2), Use in Specific Populations (8.1)] .
- Advise females of reproductive potential to use effective contraception during Otrexup therapy and for 6 months after the final dose [see Use in Specific Populations (8.3)] .
- Advise males of reproductive potential to use effective contraception during Otrexup therapy and for 3 months after the final dose [see Use in Specific Populations (8.3)] .

Infertility

Advise patients of reproductive potential that Otrexup may cause impairment of fertility, oligospermia, and menstrual dysfunction [see Warnings and Precautions (5.2), Use in Specific Populations (8.3)] .

Lactation

Advise females not to breastfeed during treatment with Otrexup and for one week after the final dose [see Use in Specific Populations (8.3)] .

Ability to Drive or Operate Machinery

Inform patients that adverse reactions such as dizziness and fatigue may affect their ability to drive or operate machinery.

Proper Storage and Disposal

Advise patients to store Otrexup at room temperature (68 to 77°F or 20 to 25°C). Inform patients and caregivers of the need for proper disposal after use, including the use of a sharps disposal container.

Address Medical Inquiries to:
Antares Pharma, Inc.
Medical Communications
100 Princeton South, Suite 300
Ewing, NJ 08628
1-855-Otrexup (1-855-687-3987)

Manufactured for:
Antares Pharma, Inc.
100 Princeton South, Suite 300
Ewing, NJ 08628 USA
Otrexup™ is the subject of US Patent Nos. 8,021,335, 6,746,429, 8,480,631, 8,562,564, 8,579,865, and 8,945,063.

©2019 Antares Pharma, Inc., Ewing, NJ 08628

Patient Package Insert

PATIENT INFORMATION

Otrexup™ (oh-TREKS-up)

(methotrexate)

injection, for subcutaneous use

What is Otrexup?

Otrexup is a single-dose auto-injector containing a prescription medicine, methotrexate.
Methotrexate is used to:

- treat certain adults with severe, active rheumatoid arthritis (RA), and children with active polyarticular juvenile idiopathic arthritis (pJIA), after treatment with other medicines including non-steroidal anti-inflammatory (NSAIDS) have been used and did not work well.
- control the symptoms of severe, resistant, disabling psoriasis in adults when other types of treatment have been used and did not work well.

Otrexup is available in doses of 10, 12.5, 15, 17.5, 20, 22.5 and 25 mg. Your doctor will prescribe a different way to take methotrexate if you need to take methotrexate by mouth or in some other way. Your doctor may also change your prescription if your dose does not match the available Otrexup doses, such as doses of less than 10 mg, more than 25 mg, or doses in between the available Otrexup doses.

Otrexup should not be used for the treatment of cancer.

Otrexup should not be used for the treatment of children with psoriasis.

What is the most important information I should know about Otrexup?

Otrexupcan cause serious side effects that can lead to death, including:

1. Organ system toxicity.People who use methotrexate for the treatment of cancer, psoriasis, or rheumatoid arthritis, have an increased risk of death from organ toxicity. Types of organ toxicity can include:

o gastrointestinal

o bone marrow

o liver

o immune system

o nerve

o lung

o kidneys

o skin

Your doctor will do blood tests and other types of tests before you take and while you are taking Otrexup to check for signs and symptoms of organ toxicity. Call your doctor right away if you have any of the following symptoms of organ toxicity:

o vomiting

o diarrhea

o mouth sores

o fever

o confusion

o weakness

o temporary blindness

o seizures

o headache

o back pain

o neck stiffness

o paralysis

o irritability

o sleepiness

o problems with coordination

o dry cough

o trouble breathing

o severe skin rash

2. Women who are pregnant are at increased risk for death of the baby and birth defects.Women who are pregnant or who plan to become pregnant must not take Otrexup.A pregnancy test should be performed before starting Otrexup.

Contraception should be used by both females and males while taking Otrexup. Pregnancy should be avoided if either partner is receiving Otrexup:

- for a minimum of 3 months after treatment with Otrexup for males.
- during and for 6 months after treatment with Otrexup for females.

Who should not take Otrexup?

Do not take Otrexup if you:

- are pregnant or planning to become pregnant. See “What is the most important information I should know about Otrexup?"
- are breastfeeding.
- Otrexup can pass into your breast milk and may harm your baby. Do notbreastfeed while taking Otrexup. Talk to your doctor about the best way to feed your baby if you take Otrexup.
- have alcohol problems (alcoholism).
- have liver problems.
- have problems fighting infection (immunodeficiency syndrome).
- have been told you have (or think you have) a blood disorder such as low levels of white blood cells, red blood cells (anemia), or platelets.
- have had an allergy to methotrexate or any of the ingredients in Otrexup. See the end of this leaflet for a complete list of ingredients in Otrexup.

Talk to your doctor before taking this medicine if you have any of these conditions.

What should I tell my doctor before taking Otrexup?

Before you take Otrexup, tell your doctor if youhave any other medical conditions.

Tell your doctor about all of the medicines you take, including prescription, over-the-counter medicines, vitamins, and herbal supplements.

Otrexup may affect how other medicines work, and other medicines may affect how Otrexup works causing side effects.

Ask your doctor or pharmacist for a list of medicines if you are not sure.

Know the medicines you take. Keep a list of them to show your doctor and pharmacist when you get a new medicine.

How should I take Otrexup?

- Read the Instructions for Use that come with Otrexup.
- Take Otrexup exactly as your doctor tells you to take it.
- Inject Otrexup only 1 time each week. Do nottake Otrexup every day.
  Taking Otrexup every day may cause death from toxicity.
- Your doctor will show you or your caregiver how to inject Otrexup. You should not inject Otrexup until you have been trained on the right way to use it.
- Check Otrexup before you inject it. Otrexup should be yellow in color and should not have any lumps or particles in it.
- Otrexup should be injected in the stomach (abdomen) or thigh.
- Do notinject Otrexup within 2 inches of the belly button (navel).
- Do notinject Otrexup in the arms or any other areas of the body.
- Do notinject Otrexup in areas where the skin is tender, bruised, red, scaly, hard, or has scars or stretch marks.
- If you are not sure if Otrexup was injected, or if you have hard time giving the injection, do notinject another dose. Call your pharmacist or doctor right away.
- If you inject too much Otrexup, call your doctor or go to the nearest hospital emergency room right away.

What should I avoid while taking Otrexup?

- Do not drink alcohol while taking Otrexup. Drinking alcohol can increase your chances of getting serious side effects.
- Otrexup can cause dizziness and tiredness. Do not drive a car, operate machinery, or do anything that needs you to be alert until you know how Otrexup affects you.
- Certain vaccinations should be avoided while taking Otrexup. Talk to your doctor before you or members of your household receive any vaccines.

What are the possible side effects of Otrexup?

Otrexup may cause serious side effects, including:

See “What is the most important information I should know about Otrexup?"

- fertility problems.Methotrexate, the active ingredient in Otrexup, may affect your ability to have a baby. Males may have a decreased sperm count, and females may have changes to their menstrual cycle. This can happen while taking Otrexup and for a short period of time after you stop.
- certain cancers.Some people who have taken methotrexate have had a certain type of cancer called Non-Hodgkin’s lymphoma and other tumors. Your doctor may tell you to stop taking Otrexup if this happens.
- tissue and bone problems.Taking Methotrexate while having radiation therapy may increase the risk of your tissue or bone not receiving enough blood. This may lead to death of the tissue or bone.

Common side effects of Otrexup include:

• nausea

• stomach pain

• indigestion (dyspepsia)

• mouth sores

• rash

• stuffy or runny nose and sore throat

• diarrhea

• abnormal liver function tests

• vomiting

• headache

• bronchitis

• low red, white, and platelet blood cell count

• hair loss

• dizziness

• sensitivity to light

• burning skin lesions

• lung problems

Tell your doctor if you have any side effect that bothers you or that does not go away.

These are not all the possible side effects of Otrexup. For more information, ask your doctor or pharmacist.

Call your doctor for medical advice about side effects. You may report side effects to FDA at 1-800-FDA-1088.

How should I dispose of Otrexup?

- Do not throw away in the household trash.Put used Otrexup in a FDA-cleared sharps disposal container right away after use.
- If you do not have a FDA-cleared sharps disposal container, you may use a household container that is:
  - made of a heavy-duty plastic
  - can be closed with a tight-fitting, puncture-resistant lid, without sharps being able to come out
  - upright stable during use
  - leak-resistant
  - properly labeled to warn of hazardous waste inside the container
- When your sharps disposal container is almost full, you will need to follow your community guidelines for the right way to dispose of your sharps disposal container. There may be state or local laws about how you should throw away used needles and syringes. For more information about the safe sharps disposal, and for specific information about sharps disposal in the state that you live in, go to the FDA’s website at: http://www.fda.gov/safesharpsdisposal.
- Do not dispose of your used sharps disposal container in your household trash unless your community guidelines permit this. Do not recycle your used sharps disposal container.
- Safely dispose of Otrexup that is out of date or is no longer needed.

How should I store Otrexup?

Store Otrexup at room temperature between 68°F to 77°F (20°C to 25°C).

- Do not freeze
- Keep Otrexup out of the light.

Keep Otrexup and all medicines out of the reach of children.

General information about the safe and effective use of Otrexup.

Methotrexate is sometimes prescribed for purposes other than those listed in Patient Information leaflet. Do not use Otrexup for a condition for which it was not prescribed. Do not give Otrexup to other people, even if they have the same symptoms that you have. It may harm them.

This Patient Information leaflet summarizes the most important information about Otrexup. If you would like more information, talk to your doctor. You can ask your doctor or pharmacist for information about Otrexup that is written for health professionals.

For more information, go to www.Otrexup.com or call 1-855-Otrexup (1-855-687-3987).

What are the ingredients in Otrexup?

Active ingredient:methotrexate

Inactive ingredients:hydrochloric acid, sodium chloride, sodium hydroxide and water for injection, USP.

This Patient Information has been approved by the U.S. Food and Drug Administration.

Manufactured for:
Antares Pharma, Inc.
100 Princeton South, Suite 300
Ewing, NJ 08628 USA
©2019 Antares Pharma, Inc., Ewing, NJ 08628

Issued: 12/2019

Instructions for Use

Read this Instructions for Use before using Otrexup™ (oh-TREKS-up) (methotrexate) injection, for subcutaneous use

Prepare to Use Otrexup

- Do not remove cap (marked 1) or safety clip (marked 2) until you are ready to inject Otrexup.
- Wash your hands well with soap and warm water.
- Check the expiration date on the label. Do notuse if expired.
- Check the seal. Do notuse Otrexup if the seal is broken (See Figure B).
- In addition to Otrexup, you will need the following items: 1 alcohol swab and 1 cotton ball or gauze.

Check the Liquid

- Look at the viewing window (See Figure C).
- The liquid should be yellow in color and should not have any lumps or particles in it.
- You may see an air bubble. This is normal.

Choose an Injection Site

- Otrexup should be injected into the stomach (abdomen) or thigh. Do notinject Otrexup within 2 inches of the belly button (navel) (See Figure D).
- Do notinject Otrexup in the arms or any other areas of the body.
- Do notinject Otrexup in areas where the skin is tender, bruised, red, scaly, hard, or has scars or stretch marks.
- Wipe the area with an alcohol swab.
- Allow the skin to dry and do nottouch this area again before giving Otrexup. Do notfan or blow on the clean area.

Give your Injection

Step 1: Remove Cap (marked 1)

- Twist cap marked 1 to remove (See Figure E). This will break the seal.
- You may notice 1 or 2 drops of medicine. This is normal.
- Do nottouch the needle end with your hands or fingers. This could inject the medicine into your hand.
- Do notreplace the cap after it has been removed.
- After the cap is removed Otrexup must be used or disposed of safely (See step 5).

STEP 2: Remove the Safety Clip (marked 2)

- Flip the Safety Clip marked 2 (See Figure F).

STEP 3: Inject Otrexup

- Place needle end of Otrexup flat against thigh or stomach (abdomen) at a 90° and firmly push device against the injection site until fully depressed. You will hear a click, hold for 3 seconds(slowly count 1,2,3) (See Figure G).

- After counting to 3, remove Otrexup from the injection site. You may notice a small amount of blood or liquid at the administration site, which is normal.
- Press a cotton ball or gauze on the area for 10 seconds. Do notrub the area.

Step 4: Check the Viewing Window

- Check the viewing window (See Figure H).
- The viewing window will be half blocked with a redflag to show that the full dose was delivered. (See Figure H).
- Dispose of Otrexup in a puncture-proof disposable container (See Step 5).
- If the viewing window is not half blocked with a red flag, call your doctor or pharmacist, or call 1-855-Otrexup (1-855-687-3987) for help.
- Do notuse another Otrexup without talking to your doctor.

Step 5:

Dispose of Otrexup

- Do not throw away in the household trash. Put used Otrexup in a FDA-cleared sharps disposal container right away after use.
- If you do not have a FDA-cleared sharps disposal container, you may use a household container that is:
  - made of a heavy-duty plastic
  - can be closed with a tight-fitting, puncture-resistant lid, without sharps being able to come out
  - upright and stable during use
  - leak-resistant
  - properly labeled to warn of hazardous waste inside the container
- When your sharps disposal container is almost full, you will need to follow your community guidelines for the right way to dispose of your sharps disposal container. There may be state or local laws about how you should throw away used needles and syringes. For more information about the safe sharps disposal, and for specific information about sharps disposal in the state that you live in, go to the FDA’s website at: http://www.fda.gov/safesharpsdisposal.
- Do not dispose of your used sharps disposal container in your household trash unless your community guidelines permit this. Do not recycle your used sharps disposal container.
- Safely dispose of Otrexup that is out of date or no longer needed.

How should I store Otrexup?

- Store Otrexup at room temperature between 68°F to 77°F (20°C to 25°C). Do not freeze.
- Keep Otrexup out of the light.

This Instructions for Use has been approved by the U.S. Food and Drug Administration.

Mfd. For Antares Pharma, Inc. Ewing, NJ 08628

12/2019

PII-13-001 V11